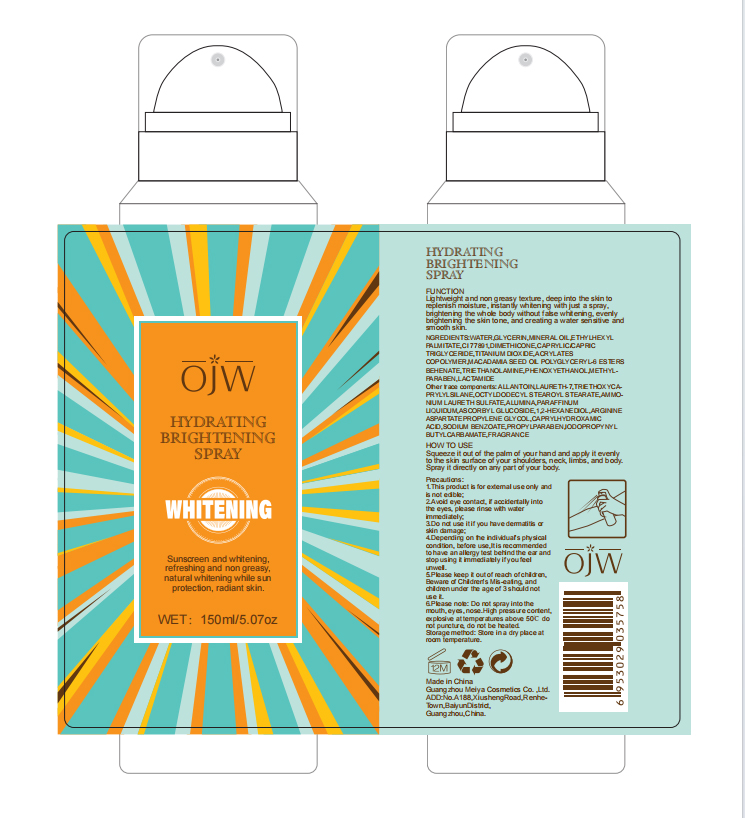 DRUG LABEL: skin whitening
NDC: 84673-002 | Form: EMULSION
Manufacturer: Guangzhou Meiya Cosmetics Co., Ltd.
Category: otc | Type: HUMAN OTC DRUG LABEL
Date: 20240903

ACTIVE INGREDIENTS: ASCORBYL GLUCOSIDE 1.5 g/1 mg
INACTIVE INGREDIENTS: LAURETH-7 0.05 g/1 mg; DIMETHICONE 1 g/1 mg; OCTYLDODECYL STEAROYL STEARATE 8 g/1 mg; GLYCERIN 8 g/1 mg; MINERAL OIL 5.1 g/1 mg; ETHYLHEXYL PALMITATE 4 g/1 mg; TRIETHOXYCAPRYLYLSILANE 1 g/1 mg; ARGININE ASPARTATE 0.5 g/1 mg; CAPRYLHYDROXAMIC ACID 0.2 g/1 mg; PHENOXYETHANOL 0.3 g/1 mg; METHYLPARABEN 0.2 g/1 mg; PROPYLPARABEN 0.1 g/1 mg; IODOPROPYNYL BUTYLCARBAMATE 2 g/1 mg; SODIUM BENZOATE 0.5 g/1 mg; WATER 73.86 g/1 mg; 1,2-HEXANEDIOL 1.4 g/1 mg; TITANIUM DIOXIDE 0.67 g/1 mg; LACTAMIDE 0.2 g/1 mg; ALLANTOIN 0.1 g/1 mg

ACTIVE INGREDIENT

ASCORBYL GLUCOSIDE 6%
CI 77891 1.96%

PURPOSE

Function: Lightweight and non greasy texture, deep into the skin to replenish moisture, instantly whitening with just a spray, brightening the whole body without false whitening, evenly brightening the skin tone, and creating a water sensitive and smooth skin.

INDICATIONS AND USAGE

How to use: Squeeze it out of the palm of your hand and apply it evenly to the skin surface of your shoulders, neck, limbs, and body. Spray it directly on any part of your body.

WARNINGS

Precautions:

1. This product is for external use only and is not edible;

2. Avoid eye contact, if accidentally into the eyes, please rinse with water immediately;

3. Do not use it if you have dermatitis or skin damage;

4. Depending on the individual's physical condition, before use,It is recommended to have an allergy test behind the ear and stop using it immediately if you feel unwell.

5. Please keep it out of reach of children, Beware of Children's Mis-eating, and children under the age of 3 should not use it.

6.Please note: Do not spray into the mouth, eyes, nose.High pressure content, explosive at temperatures above 50℃ do not puncture, do not be heated.

STOP USE

Depending on the individual's physical condition, before use,It is recommended to have an allergy test behind the ear and stop using it immediately if you feel unwell.

DO NOT USE

1. Avoid eye contact, if accidentally into the eyes, please rinse with water immediately;

2. Do not use it if you have dermatitis or skin damage;

3.Depending on the individual's physical condition, before use,It is recommended to have an allergy test behind the ear and stop using it immediately if you feel unwell.

KEEP OUT OF REACH OF CHILDREN

Please keep it out of reach of children, Beware of Children's Mis-eating, and children under the age of 3 should not use it.

WHEN USING

1.This product is for external use only and is not edible
2.Avoid eye contact, if accidentally into the eyes, please rinse with water immediately;

3. Do not use it if you have dermatitis or skin damage;

4. Depending on the individual's physical condition, before use,It is recommended to have an allergy test behind the ear and stop using it immediately if you feel unwell.

5. Please keep it out of reach of children, Beware of Children's Mis-eating, and children under the age of 3 should not use it.

6.Please note: Do not spray into the mouth, eyes, nose.High pressure content, explosive at temperatures above 50℃ do not puncture, do not be heated.

INACTIVE INGREDIENT

WATER 7732-18-5 73.86
GLYCERIN 56-81-5 8
MINERAL OIL 64742-54-7 5.1
ETHYLHEXYL PALMITATE 29806-73-3 4
WATER 7732-18-5 2.5
ACRYLATES COPOLYMER 25133-97-5 / 25035-69-2 2.5
LAURETH-7 3055-97-8 / 68439-50-9 / 9002-92-0 2.5
AMMONIUM LAURETH SULFATE 32612-48-9 / 67762-19-0 2.5
SODIUM BENZOATE 532-32-1 2.5
CI 77891 13463-67-7 2
TRIETHOXYCAPRYLYLSILANE 2943-75-1 2
ALUMINA 1344-28-1 2
CAPRYLIC/CAPRIC TRIGLYCERIDE 73398-61-5/ 65381-09-1 1
DIMETHICONE 63148-62-9 / 9006-65-9 / 9016-00-6 1
TITANIUM DIOXIDE 13463-67-7 0.7
TRIETHOXYCAPRYLYLSILANE 2943-75-1 0.7
LACTAMIDE Lactamide 2043-43-8 0.4
WATER 7732-18-5 0.4
1,2-HEXANEDIOL 6920-22-5 0.4
ARGININE ASPARTATE 7675-83-4 0.4
PROPYLENE GLYCOL 57-55-6 0.4
CAPRYLHYDROXAMIC ACID 7377/3/9 0.4
MACADAMIA SEED OIL POLYGLYCERYL-6 ESTERS BEHENATE / 0.4
OCTYLDODECYL STEAROYL STEARATE 90052-75-8 0.4
PARAFFINUM LIQUIDUM 8012-95-1 / 8042-47-5 0.4
PHENOXYETHANOL 122-99-6 0.3
IODOPROPYNYL BUTYLCARBAMATE 55406-53-6 0.3
TRIETHANOLAMINE 102-71-6 0.3
METHYLPARABEN 99-76-3 0.2
ALLANTOIN 97-59-6 0.1
PROPYLPARABEN 94-13-3 0.1
FRAGRANCE - 0.04